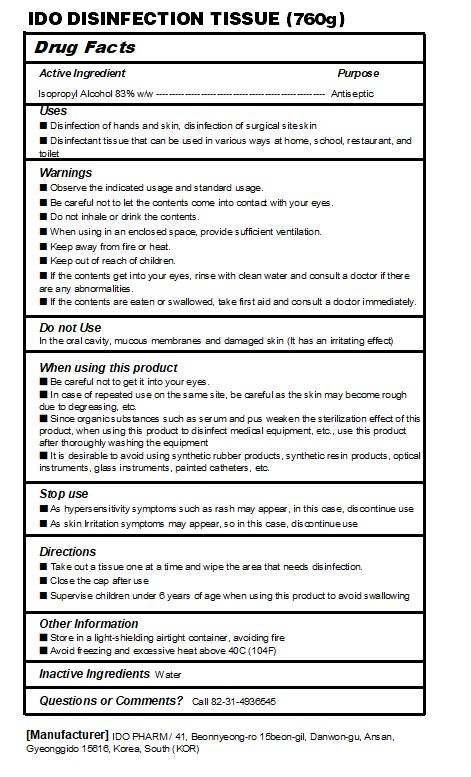 DRUG LABEL: IDO DISINFECTION TISSUE
NDC: 77039-021 | Form: LIQUID
Manufacturer: IDO PHARM
Category: otc | Type: HUMAN OTC DRUG LABEL
Date: 20220602

ACTIVE INGREDIENTS: ISOPROPYL ALCOHOL 83 mL/100 g
INACTIVE INGREDIENTS: WATER

ACTIVE INGREDIENT

Isopropyl Alcohol

INACTIVE INGREDIENT

Water

PURPOSE

■ Disinfection of hands and skin, disinfection of surgical site skin
■ Disinfectant tissue that can be used in various ways at home, school, restaurant, and toilet

Keep out of reach of children

INDICATIONS AND USAGE

■ Take out a tissue one at a time and wipe the area that needs disinfection.
■ Close the cap after use
■ Supervise children under 6 years of age when using this product to avoid swallowing

WARNINGS

■ Observe the indicated usage and standard usage.
■ Be careful not to let the contents come into contact with your eyes.
■ Do not inhale or drink the contents.
■ When using in an enclosed space, provide sufficient ventilation.
■ Keep away from fire or heat.
■ Keep out of reach of children.
■ If the contents get into your eyes, rinse with clean water and consult a doctor if there are any abnormalities.
■ If the contents are eaten or swallowed, take first aid and consult a doctor immediately.

DOSAGE AND ADMINISTRATION

topical use only